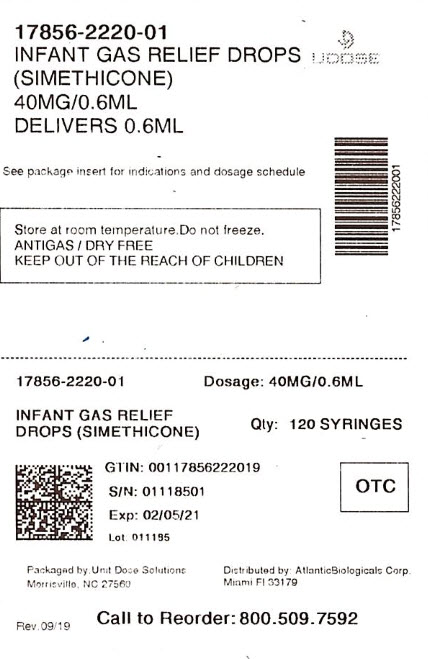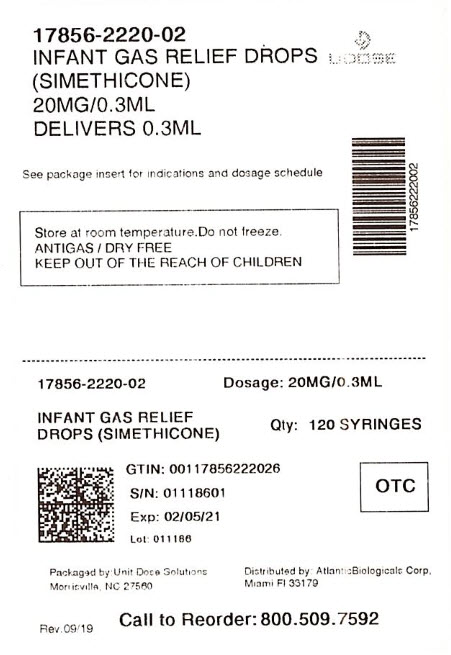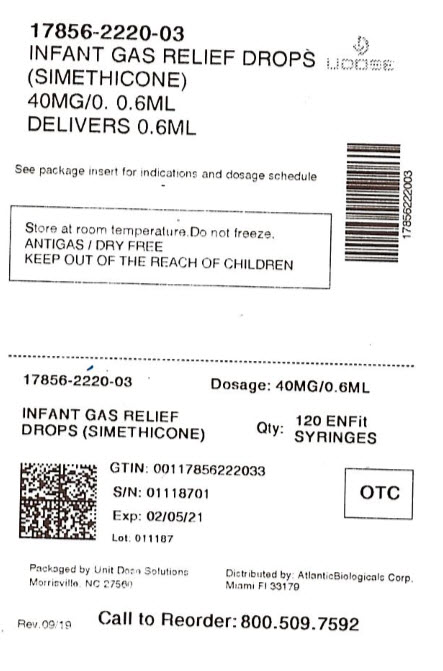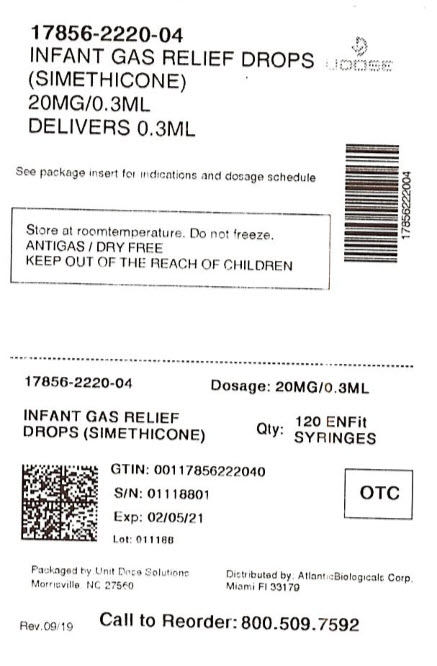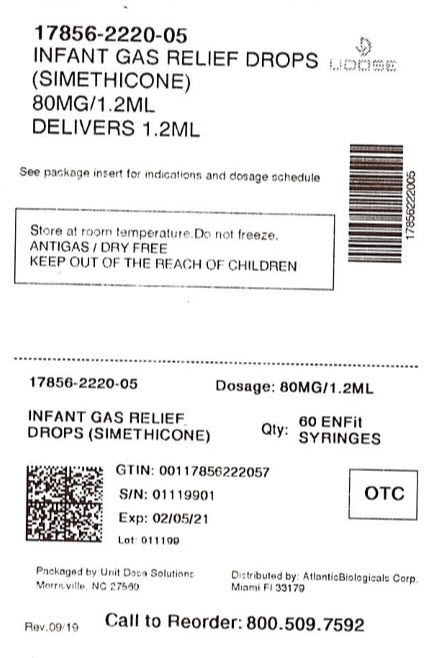 DRUG LABEL: Gas Relief
NDC: 17856-2220 | Form: SUSPENSION/ DROPS
Manufacturer: ATLANTIC BIOLOGICALS CORP.
Category: otc | Type: HUMAN OTC DRUG LABEL
Date: 20200817

ACTIVE INGREDIENTS: DIMETHICONE 20 mg/0.3 mL
INACTIVE INGREDIENTS: CARBOXYMETHYLCELLULOSE SODIUM; ANHYDROUS CITRIC ACID; MALTITOL; CELLULOSE, MICROCRYSTALLINE; WATER; SODIUM BENZOATE; SODIUM CITRATE; XANTHAN GUM

Rugby infant drops

Active ingredient (in each 0.3 mL)

Simethicone 20 mg

Purpose

Antigas

Use

relieves the symptoms referred to as gas

Warnings

Keep out of reach of children. In case of overdose, get medical help or contact a poison control center right away.

Directions

- shake well before using
- all dosages may be repeated as needed, after meals and at bedtime, or as directed by a physician
- do not exceed 12 doses per day
- fill enclosed dropper to recommended dosage level and dispense liquid slowly into baby’s mouth, toward inner cheek
- may be mixed with 1 oz of water, infant formula or other suitable liquid
- for best results, clean dropper after each use and replace original cap

Age (years) | Weight (lbs) | Dose
infants (under 2) | under 24 | 0.3 mL
children (over 2) | over 24 | 0.6 mL

Other information

- store at room temperature
- do not freeze
- see bottom panel for lot number and expiration date
- TAMPER-EVIDENT: Do not use if foil seal under cap is broken or missing

Inactive ingredients

carboxymethylcellulose sodium, citric acid, flavor, maltitol, microcrystalline cellulose, purified water, sodium benzoate, sodium citrate, xanthan gum.

Questions or comments?

1-800-645-2158

DISTRIBUTED BY:

ATLANTIC BIOLOGICALS CORP.

MIAMI, FL 33179